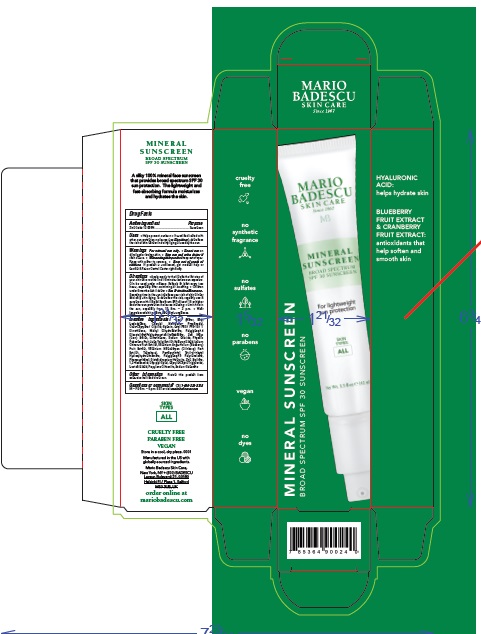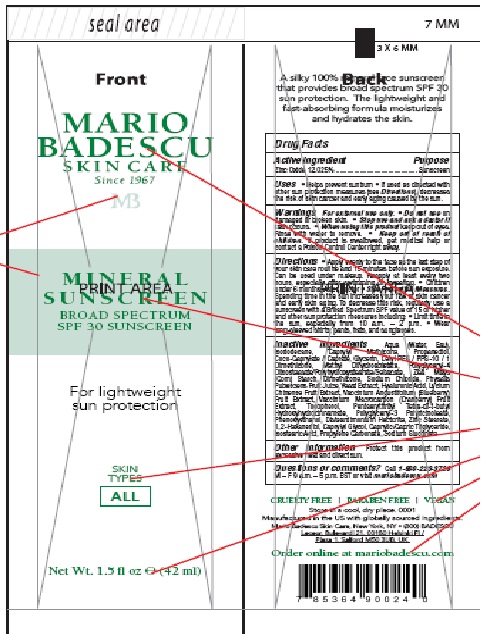 DRUG LABEL: Mineral Sunscreen
NDC: 54111-183 | Form: CREAM
Manufacturer: Bentley Laboratories LLC
Category: otc | Type: HUMAN OTC DRUG LABEL
Date: 20241015

ACTIVE INGREDIENTS: ZINC OXIDE 12.025 g/100 mL
INACTIVE INGREDIENTS: WATER; ISODODECANE; CAPRYLYL TRISILOXANE; PROPANEDIOL; COCO-CAPRYLATE/CAPRATE; GLYCERIN; CETYL PEG/PPG-10/1 DIMETHICONE (HLB 4); METHYL DIHYDROABIETATE; POLYGLYCERYL-4 DIISOSTEARATE/POLYHYDROXYSTEARATE/SEBACATE; STARCH, CORN; DIMETHICONE; SODIUM CHLORIDE; PHYSALIS PUBESCENS FRUIT JUICE; YEAST, UNSPECIFIED; HYALURONIC ACID; LYCIUM CHINENSE FRUIT; LOWBUSH BLUEBERRY; CRANBERRY; TOCOPHEROL; PENTAERYTHRITOL TETRAKIS(3-(3,5-DI-TERT-BUTYL-4-HYDROXYPHENYL)PROPIONATE); POLYGLYCERYL-3 PENTARICINOLEATE; PHENOXYETHANOL; DISTEARDIMONIUM HECTORITE; ZINC STEARATE; 1,2-HEXANEDIOL; CAPRYLYL GLYCOL; MEDIUM-CHAIN TRIGLYCERIDES; ISOSTEARIC ACID; PROPYLENE CARBONATE; SODIUM GLUCONATE

MARIO BADESCU
MINERAL SUNSCREEN BROAD SPECTRUM SPF 30 SUNSCREEN

Drug Facts

Active ingredient

Zinc Oxide 12.025%

Purpose

Sunscreen

INDICATIONS AND USAGE

Uses • Helps prevent sunburn• If used as directed with
other sun protection measures (see Directions), decreases
the risk of skin cancer and early aging caused by the sun.

WARNINGS

Warnings For external use only. • Do not use on
damaged or broken skin. • Stop use and ask a doctor if
rash occurs. • When using this product keep out of eyes.
Rinse with water to remove.

Keep out of reach of children.

If product is swallowed, get medical help or
contact a Poison Control Center right away.

DOSAGE AND ADMINISTRATION

Directions • Apply evenly to the face as the last step of
your skin care routine and 15 minutes before sun exposure.
Can be used under makeup. Reapply at least every two
hours, especially after swimming or sweating. • Children
under 6 months: Ask a doctor • Sun Protection Measures.
Spending time in the sun increases your risk of skin cancer
and early skin aging. To decrease this risk, regularly use a
sunscreen with a Broad Spectrum SPF value of 15 or higher
and other sun protection measures including: • Limit time in
the sun, especially from 10 a.m. – 2 p.m. • Wear
long-sleeved shirts, pants, hats, and sunglasses.

Inactive ingredients Aqua (Water, Eau),
Isododecane, Caprylyl Methicone, Propanediol,
Coco-Caprylate / Caprate, Glycerin, Cetyl PEG / PPG-10 / 1
Dimethicone, Methyl Dihydroabietate, Polyglyceryl-4
Diisostearate/Polyhydroxystearate/Sebacate, Zea Mays
(Corn) Starch, Dimethicone, Sodium Chloride, Physalis
Pubescens Fruit Juice, Yeast Extract, Hyaluronic Acid, Lycium
Chinense Fruit Extract, Vaccinium Angustifolium (Blueberry)
Fruit Extract, Vaccinium Macrocarpon (Cranberry) Fruit
Extract, Tocopherol, Pentaerythrityl Tetra-di-t-butyl
Hydroxyhydrocinnamate, Polyglyceryl-3 Polyricinoleate,
Phenoxyethanol, Disteardimonium Hectorite, Zinc Stearate,
1,2-Hexanediol, Caprylyl Glycol, Caprylic/Capric Triglyceride,
Isostearic Acid, Propylene Carbonate, Sodium Gluconate

Other informationProtect this product from
excessive heat and direct sun.

Questions or comments?Call 1-800-223-3728
M – F 9 a.m. – 5 p.m. EST or visit mariobadescu.com

Mario Badescu Mineral Sunscreen SPF 30 product label

MARIO
BADESCU
SKIN CARE
Since 1967
MB

MINERAL

SUNSCREEN

BROAD SPECTRUM

SPF 30 SUNSCREEN

Store in a cool, dry place. 0001
Manufactured in the US with
globally-sourced ingredients.
Mario Badescu Skin Care,
New York, NY • (800) BADESCU
Leceur, Bulevardi 21, 00180
Helsinki FI / Plaza 1, Salford
M50 3UB, UK

order online at
mariobadescu.com

res